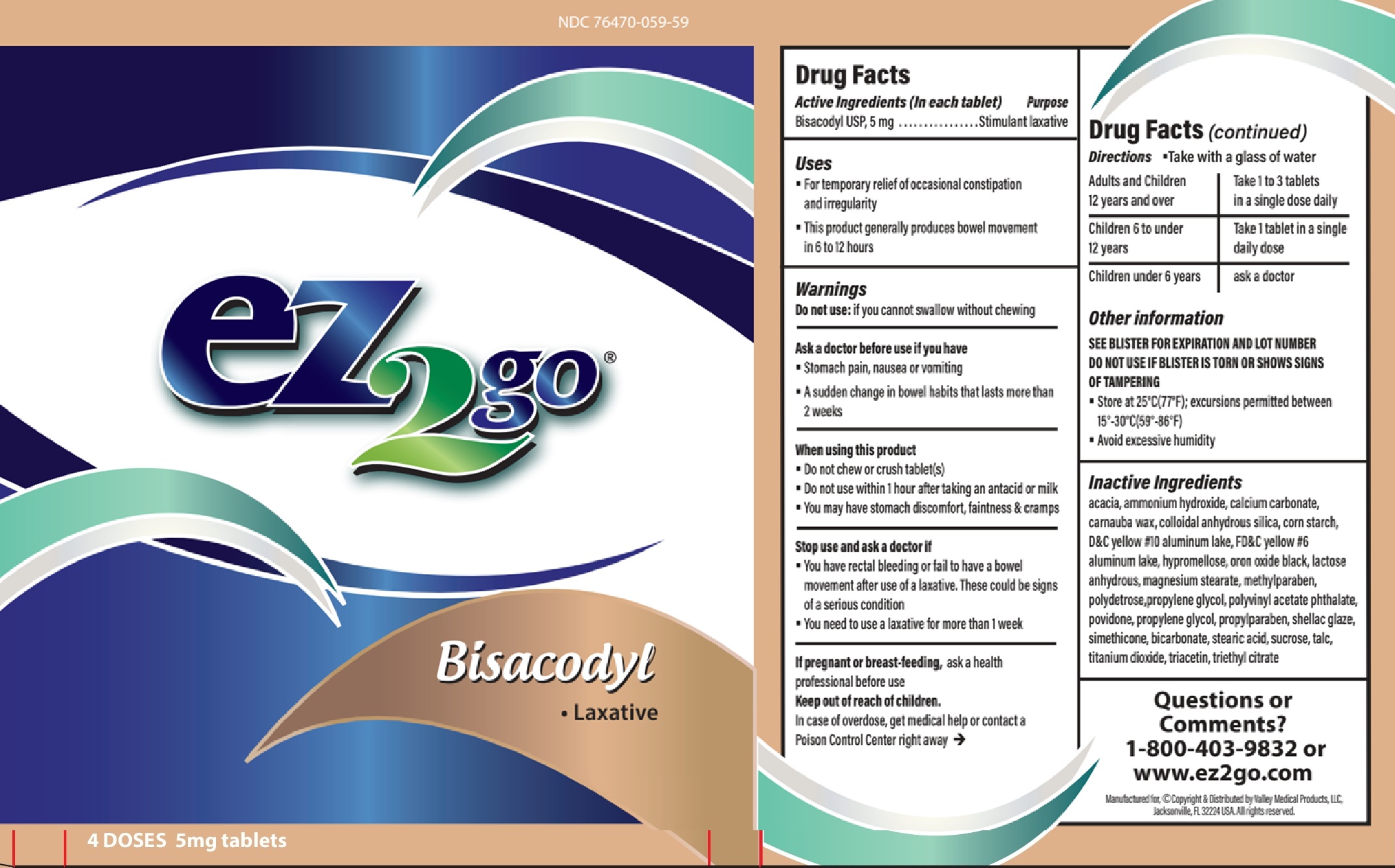 DRUG LABEL: ez2go Laxative Bisacodyl
NDC: 76470-059 | Form: CAPSULE, COATED
Manufacturer: Valley Medical Products, LLC
Category: otc | Type: HUMAN OTC DRUG LABEL
Date: 20260126

ACTIVE INGREDIENTS: BISACODYL 5 mg/1 1
INACTIVE INGREDIENTS: ACACIA; AMMONIA; CALCIUM CARBONATE; CARNAUBA WAX; STARCH, CORN; D&C YELLOW NO. 10 ALUMINUM LAKE; FD&C YELLOW NO. 6 ALUMINUM LAKE; HYPROMELLOSE, UNSPECIFIED; ANHYDROUS LACTOSE; MAGNESIUM STEARATE; METHYLPARABEN; PROPYLENE GLYCOL; POLYVINYL ACETATE PHTHALATE; POVIDONE; PROPYLPARABEN; BICARBONATE ION; STEARIC ACID; SUCROSE; TALC; TITANIUM DIOXIDE; TRIACETIN; TRIETHYL CITRATE

ez2go Laxative Bisacodyl

Active Ingredients (In each tablet)

Bisacodyl USB 5 mg

Purpose

Stimulant laxative

Uses

- For temporary relief of occasional constipation and irregularity
- This product generally produces bowel movement in 6 to 12 hours

Warnings

Do not use:

if you cannot swallow without chewing

Ask a doctor before use if you have

- Stomach pain, nausea or vomiting
- A sudden change in bowel habits that lasts more than 2 weeks

When using this product

- Do not chew or crush tablet(s)
- Do not use within 1 hour after taking an antacid or milk
- you may have stomach discomfort, faintness & cramps

Stop use and ask a doctor if

- You have rectal bleeding or fail to have a bowel movement after use of a laxative. These could be signs of a serious condition
- You need to use a laxative for more than 1 week

If pregnant or breast-feeding,

ask a health professional before use

Keep out of reach of children.

In case of overdose, get medical help or contact a Poison Control Center right away

Directions

- Take with a glass of water
  Adults and Children 12 years and over | Take 1 to 3 tablets in a single dose daily
  Children 6 to under 12 years | Take 1 tablet in a single daily dose
  Children under 6 years | ask a doctor

Other information

SEE BLISTER FOR EXPIRATION AND LOT NUMBER DO NOT USE IF BLISTER IS TORN OR SHOWS SIGNS OF TAMPERING

- Store at 25°C(77°F); excursions permitted between 15°-30°C(59°-86°F)
- Avoid excessive humidity
- See end flap for expiration date and lot number

Inactive Ingredients

acacia, ammonium hydroxide, calcium carbonate, carnauba wax, colloidal anhydrous silica, corn starch, D&C yellow #10 aluminum lake, FD&C yellow #6 aluminum lake, hypromellose, oron oxide black, lactose anhydrous, magnesium stearate, methylparaben, polydetrose,propylene glycol, polyvinyl acetate phthalate, povidone, propylene glycol, propylparaben, shellac glaze, simethicone, bicarbonate, stearic acid, sucrose, talc, titanium dioxide, triacetin, triethyl citrate

Questions or Comments?

1-800-403-9832 or WWW.ez2go.com